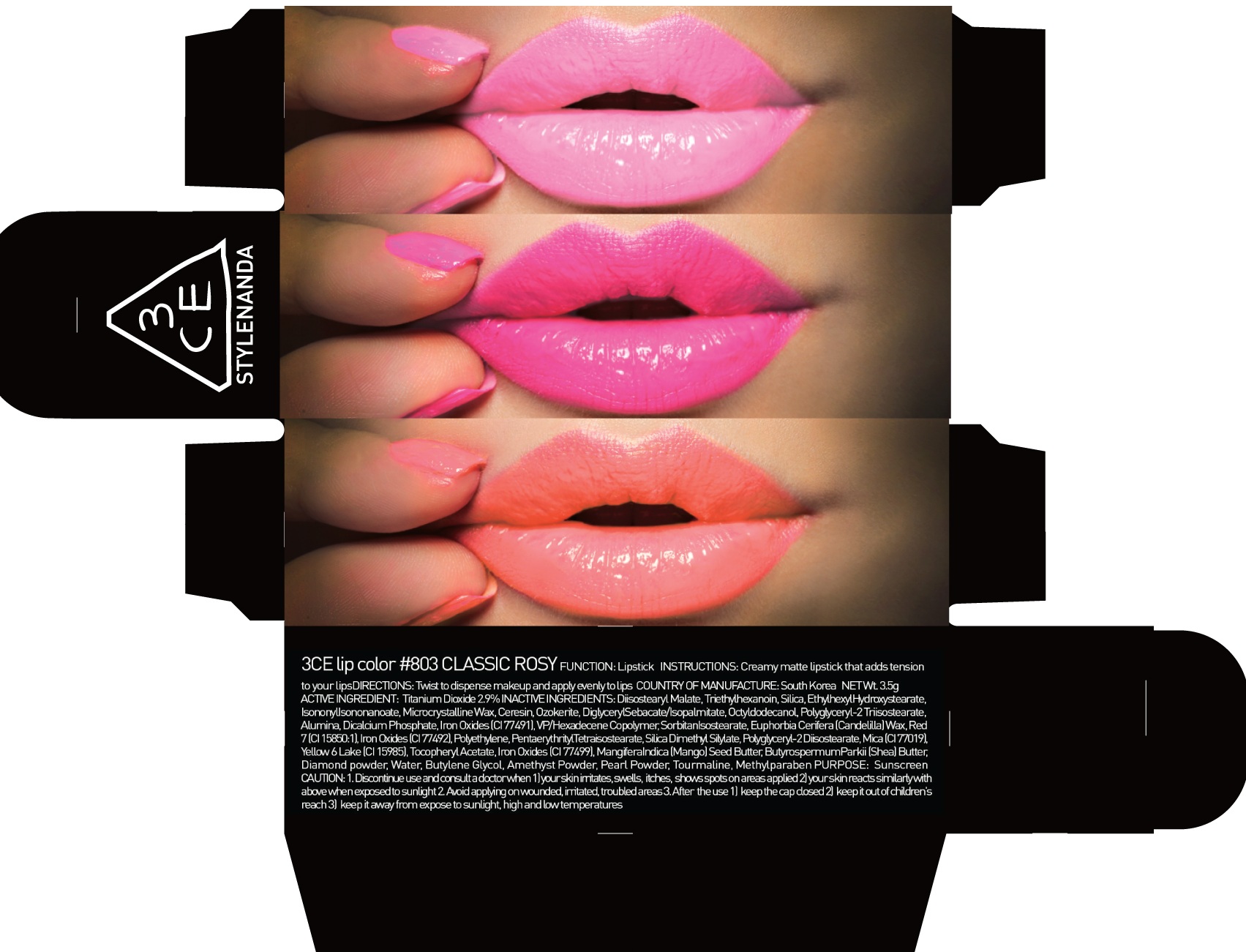 DRUG LABEL: 3CE LIP COLOR 803 CLASSIC ROSY
NDC: 60764-054 | Form: LIPSTICK
Manufacturer: Nanda Co., Ltd
Category: otc | Type: HUMAN OTC DRUG LABEL
Date: 20161004

ACTIVE INGREDIENTS: Titanium Dioxide 0.10 g/3.5 g
INACTIVE INGREDIENTS: Diisostearyl Malate; Triethylhexanoin

ACTIVE INGREDIENT

Active Ingredient: Titanium Dioxide 2.9%

INACTIVE INGREDIENT

Inactive Ingredients: Diisostearyl Malate, Triethylhexanoin, Silica, EthylhexylHydroxystearate, IsononylIsononanoate, Microcrystalline Wax, Ceresin, Ozokerite, DiglycerylSebacate/Isopalmitate, Octyldodecanol, Polyglyceryl-2 Triisostearate, Alumina, Dicalcium Phosphate, Iron Oxides (CI 77491), VP/Hexadecene Copolymer, SorbitanIsostearate, Euphorbia Cerifera (Candelilla) Wax, Red 7 (CI 15850:1), Iron Oxides (CI 77492), Polyethylene, PentaerythritylTetraisostearate, Silica Dimethyl Silylate, Polyglyceryl-2 Diisostearate, Mica (CI 77019), Yellow 6 Lake (CI 15985), Tocopheryl Acetate, Iron Oxides (CI 77499), MangiferaIndica (Mango) Seed Butter, ButyrospermumParkii (Shea) Butter, Diamond powder, Water, Butylene Glycol, Amethyst Powder, Pearl Powder, Tourmaline, Methylparaben

PURPOSE

Purpose: Sunscreen

CAUTION

CAUTION: 1. Discontinue use and consult a doctor when - your skin irritates, swells, itches, shows spots on areas applied - your skin reacts similarly with above when exposed to sunlight 2. Avoid applying on wounded, irritated, troubled areas 3. After the use - keep the cap closed - keep it out of children's reach - keep it away from expose to sunlight, high and low temperatures

DESCRIPTION

INSTRUCTIONS: A rich color lipstick that moistly adheres to lips.

Directions: Twist to dispense makeup and apply evenly to lips